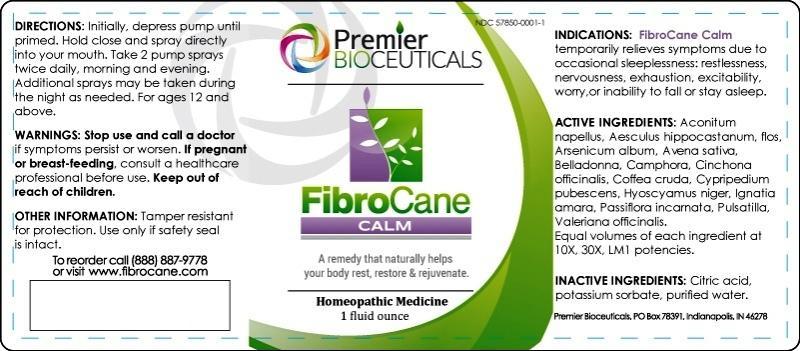 DRUG LABEL: FibroCane CALM
NDC: 57850-0001 | Form: LIQUID
Manufacturer: Premier Bioceuticals LLC.
Category: homeopathic | Type: HUMAN OTC DRUG LABEL
Date: 20140624

ACTIVE INGREDIENTS: ACONITUM NAPELLUS 10 [hp_X]/29.6 mL; AESCULUS HIPPOCASTANUM FLOWER 10 [hp_X]/29.6 mL; ARSENIC TRIOXIDE 10 [hp_X]/29.6 mL; AVENA SATIVA FLOWERING TOP 10 [hp_X]/29.6 mL; ATROPA BELLADONNA 10 [hp_X]/29.6 mL; CAMPHOR (NATURAL) 10 [hp_X]/29.6 mL; CINCHONA OFFICINALIS BARK 10 [hp_X]/29.6 mL; ARABICA COFFEE BEAN 10 [hp_X]/29.6 mL; CYPRIPEDIUM PARVIFOLUM ROOT 10 [hp_X]/29.6 mL; HYOSCYAMUS NIGER 10 [hp_X]/29.6 mL; STRYCHNOS IGNATII SEED 10 [hp_X]/29.6 mL; PASSIFLORA INCARNATA FLOWERING TOP 10 [hp_X]/29.6 mL; PULSATILLA VULGARIS 10 [hp_X]/29.6 mL; VALERIAN 10 [hp_X]/29.6 mL
INACTIVE INGREDIENTS: CITRIC ACID MONOHYDRATE; POTASSIUM SORBATE; WATER

FibroCane CALM

INDICATIONS AND USAGE

Indications: FibroCane Calm temporarily relieves symptoms due to occasional sleeplessness: restlessness, nervousness, exhaustion, excitability, worry or inability to fall or stay asleep.

ACTIVE INGREDIENT

Active Ingredients: Aconitum napellus, Aesculus hippocastanum, flos, Arsenicum album, Avena sativa, Belladonna, Camphora, Cinchona officinalis, Coffea cruda, Cypripedium pubescens, Hyoscyamus niger, Ignatia amara, Passiflora incarnata, Pulsatilla, Valeriana officinalis. Equal volumes of each ingredient at 10X, 30X, LM1 potencies.

Inactive Ingredients:

Citric acid, potassium sorbate, purified water.

DOSAGE AND ADMINISTRATION

Directions: Initially, depress pump until primed. Hold close and spray directly into your mouth. Take 2 pump sprays twice daily, morning and evening. Additional sprays may be taken during the night as needed. For ages 12 and above.

Warnings

- Stop use and call a doctor if symptoms persist or worsen.
- If pregnant or breast-feeding, consult a healthcare professional before use.

- Keep out of reach of children.

Other Information:

Tamper resistant for your protection. Use only if safety seal is intact.

PURPOSE

FibroCane Calm temporarily relieves symptoms due to occasional sleeplessness:

- restlessness
- nervousness
- exhaustion
- excitability
- worry or inability to fall or stay asleep